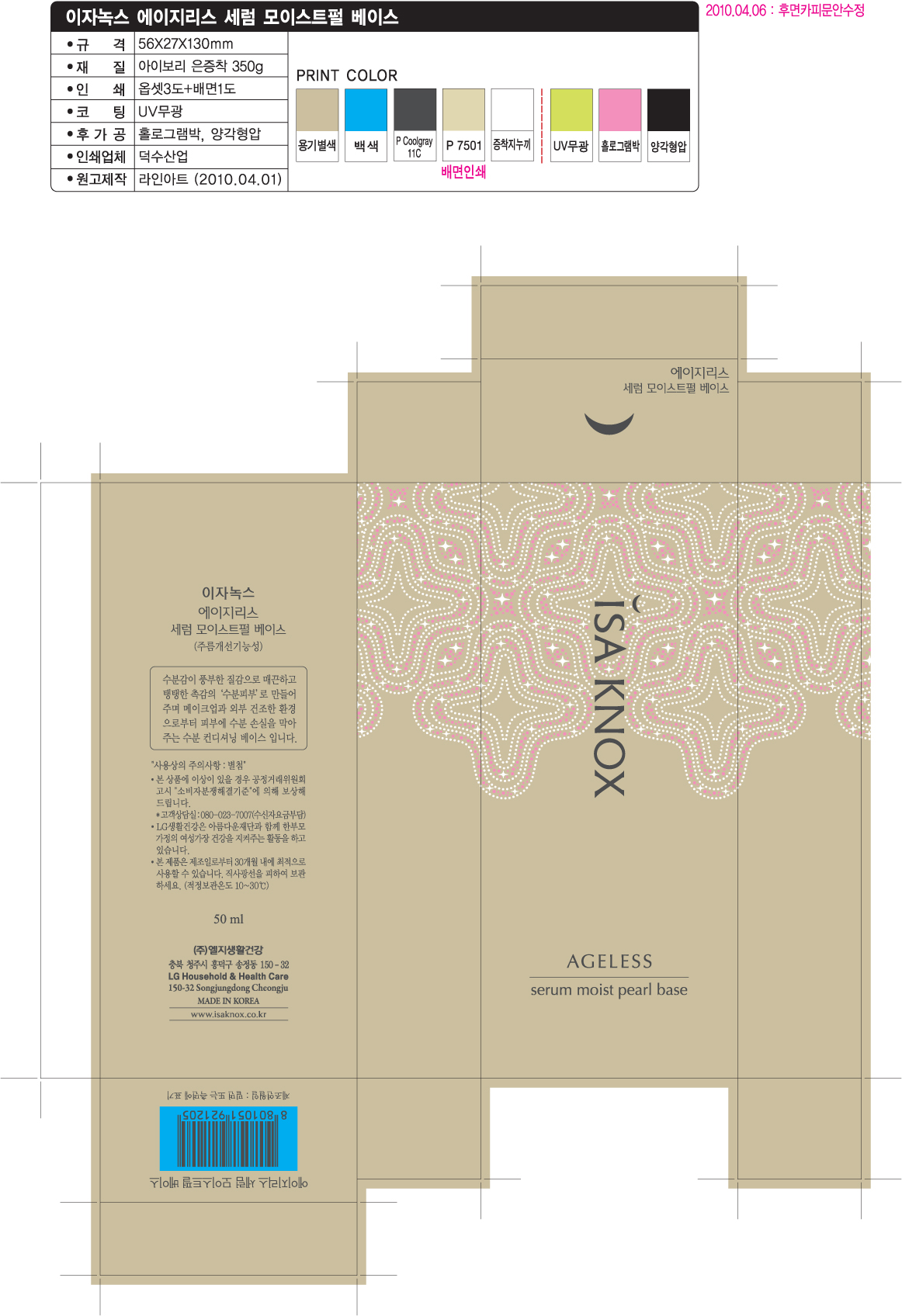 DRUG LABEL: ISAKNOX AGELESS SERUM MOIST PEARL BASE
NDC: 53208-478 | Form: LIQUID
Manufacturer: LG Household and Healthcare, Inc.
Category: otc | Type: HUMAN OTC DRUG LABEL
Date: 20120515

ACTIVE INGREDIENTS: OCTINOXATE 3 mL/100 mL; TITANIUM DIOXIDE 3.38 mL/100 mL; DIMETHICONE 0.08 mL/100 mL; ALUMINUM HYDROXIDE 0.18 mL/100 mL; STEARIC ACID 0.18 mL/100 mL; HYDROXYPROLINE 0.53 mL/100 mL
INACTIVE INGREDIENTS: WATER; CYCLOMETHICONE 5; CYCLOMETHICONE; ISODODECANE; MAGNESIUM SULFATE, UNSPECIFIED; SORBITAN; HECTORITE; PHENOXYETHANOL; METHYLPARABEN; DISTEARYLDIMONIUM CHLORIDE; STEARIC ACID; ETHYLPARABEN; PROPYLPARABEN

Drug Facts

Active Ingredients

HYDROXYPROLINE 0.5ml/100ml

WARNINGS AND PRECAUTIONS

For external use only.

Keep out of reach of children. Is swallowed, get medical help or contact a Poison Control Center right away.

WHEN USING

Keep out of eyes. Rinse with water to remove.

PACKAGE LABEL

Isaknox

Ageless

Pearl Base